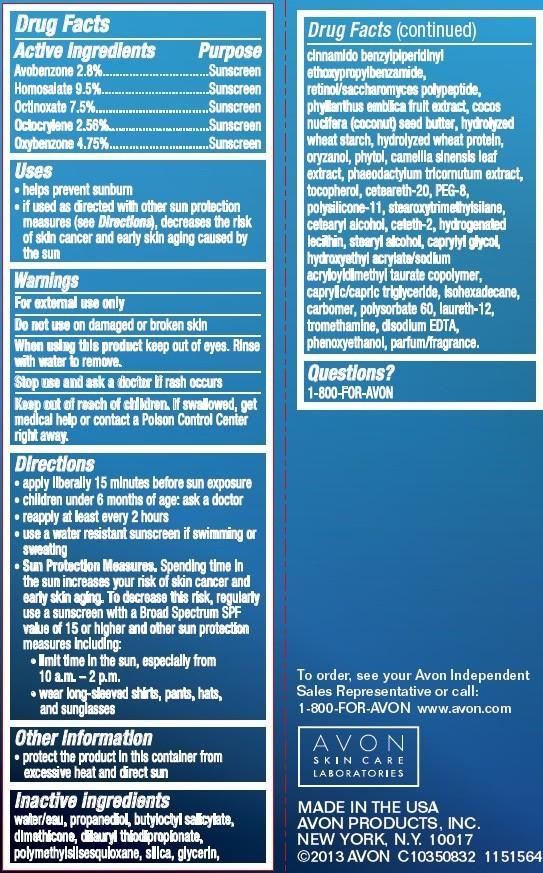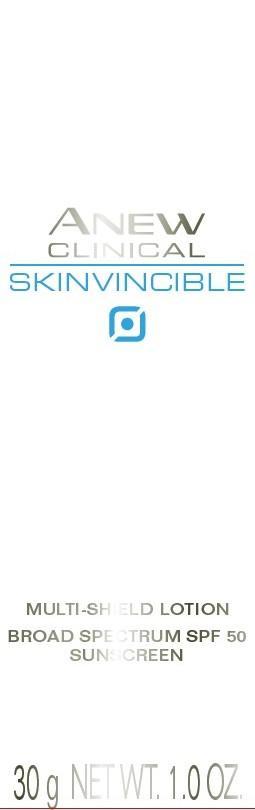 DRUG LABEL: Anew Clinical
NDC: 10096-0304 | Form: LOTION
Manufacturer: New Avon LLC
Category: otc | Type: HUMAN OTC DRUG LABEL
Date: 20190101

ACTIVE INGREDIENTS: AVOBENZONE 28 mg/1 g; HOMOSALATE 95 mg/1 g; OCTINOXATE 75 mg/1 g; OCTOCRYLENE 25.6 mg/1 g; OXYBENZONE 47.5 mg/1 g
INACTIVE INGREDIENTS: WATER

Anew Skinvincible Day Lotion Broad Spectrum SPF 50

Active ingredients
Avobenzone 2.8%...........................
Homosalate 9.5%...........................
Octinoxate 7.5%............................
Octocrylene 2.56%.......................
Oxybenzone 4.75%........................

Purpose
.................Sunscreen
.................Sunscreen
................Sunscreen
................Sunscreen
..............Sunscreen

Uses
• helps prevent sunburn
• if used as directed with other sun protection measures (see Directions), decreases the risk of skin cancer and early skin aging caused by
the sun

Warnings
For external use only

Do not use on damaged or broken skin

When using this product keep out of eyes. Rinse with water to remove.

Stop use and ask a doctor if rash occurs

Keep out of reach of children. If swallowed, get medical help or contact a Poison Control Center right away.

Directions
• apply liberally 15 minutes before sun exposure
• children under 6 months of age: ask a doctor
• reapply at least every 2 hours
• use a water resistant sunscreen if swimming or sweating
• Sun Protection Measures. Spending time in the sun increases your risk of skin cancer and early skin aging. To decrease this risk, regularly
use a sunscreen with a Broad Spectrum SPF value of 15 or higher and other sun protection measures including:
• limit time in the sun, especially from 10 a.m. – 2 p.m.
• wear long-sleeved shirts, pants, hats, and sunglasses

Inactive ingredients
water/eau, propanediol, butyloctyl salicylate, dimethicone, dilauryl thiodipropionate, polymethylsilsesquioxane, silica, glycerin, cinnamido benzylpiperidinyl ethoxypropylbenzamide, retinol/saccharomyces polypeptide, phyllanthus emblica fruit extract, cocos nucifera (coconut) seed butter, hydrolyzed wheat starch, hydrolyzed wheat protein, oryzanol, phytol, camellia sinensis leaf extract, phaeodactylum tricornutum extract, tocopherol, ceteareth-20, PEG-8, polysilicone-11, stearoxytrimethylsilane, cetearyl alcohol, ceteth-2, hydrogenated lecithin, stearyl alcohol, caprylyl glycol, hydroxyethyl acrylate/sodium acryloyldimethyl taurate copolymer, caprylic/capric triglyceride, isohexadecane, carbomer, polysorbate 60, laureth-12, tromethamine, disodium EDTA, phenoxyethanol, parfum/fragrance.

Questions?
1-800-FOR-AVON